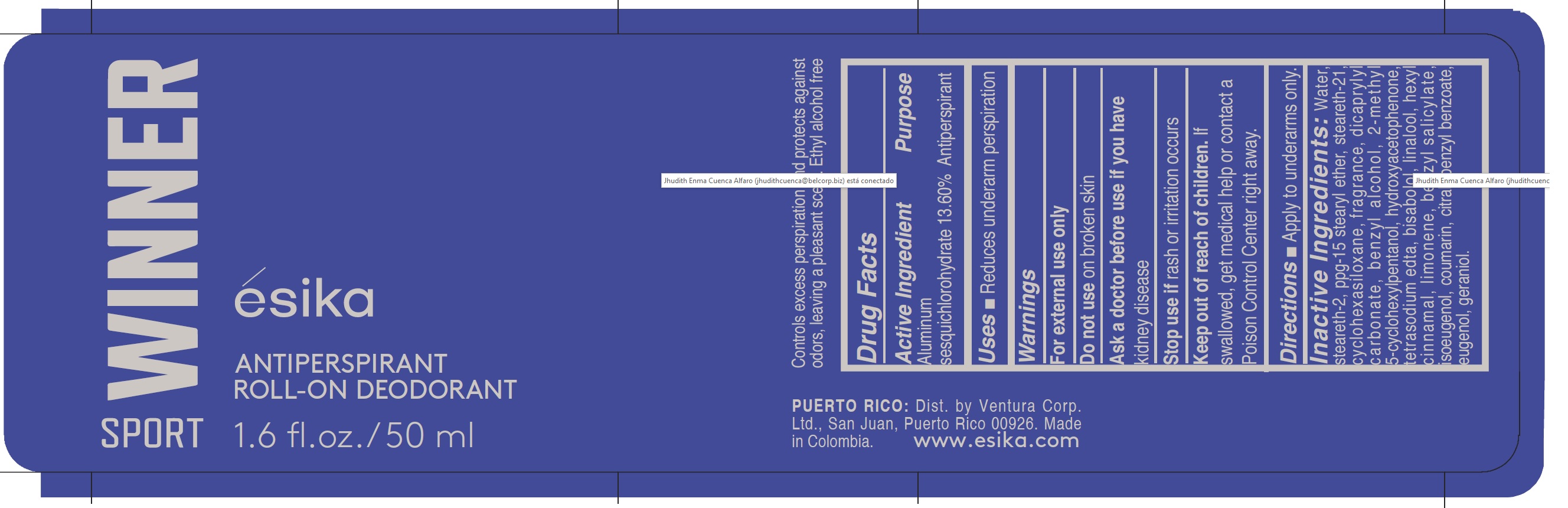 DRUG LABEL: Esika Winner Sport Antiperspirant Roll-on Deodorant
NDC: 14141-200 | Form: EMULSION
Manufacturer: Bel Star S.A. (Colombia)
Category: otc | Type: HUMAN OTC DRUG LABEL
Date: 20241028

ACTIVE INGREDIENTS: ALUMINUM SESQUICHLOROHYDRATE 13.6 g/100 mL
INACTIVE INGREDIENTS: BENZYL ALCOHOL; STEARETH-2; BENZYL BENZOATE; EUGENOL; CITRAL; LIMONENE, (+)-; .ALPHA.-HEXYLCINNAMALDEHYDE; GERANIOL; BENZYL SALICYLATE; ISOEUGENOL; COUMARIN; 2-METHYL 5-CYCLOHEXYLPENTANOL; DICAPRYLYL CARBONATE; CYCLOMETHICONE 6; PPG-15 STEARYL ETHER; STEARETH-21; LINALOOL, (+)-; WATER; HYDROXYACETOPHENONE; EDETATE SODIUM; LEVOMENOL

Esika Winner Sport Antiperspirant Roll-on Deodorant

Active Ingredient Purpose

Aluminum sesquichlorohydrate 13.60% Antiperspirant

Uses

- reduces underarm perspiration

Keep out of reach of children. If swallowed, get medical help or contact a Poison Control Center right away.

Stop use if rash or irritation occurs

Warnings

For external use only

Do not use on broken skin

Ask a doctor before use if you have kidney disease

Directions

Apply to underarms only

Inactive Ingredients:

water, steareth-2,ppg-15 stearyl ether, steareth-21, cyclohexasiloxane, fragrance, dicaprylyl carbonate, benzyl alcohol, 2-methyl 5-cyclohexylpentanol, hydroxyacetophenone, tetrasodium edta, bisabolol, linalool, hexyl cinnamal, limonene, benzyl salicylate, isoeugenol, coumarin, citral, benzyl benzoate, eugenol, geraniol.

PACKAGE LABEL

Esika Winner Sport Antiperspirant Roll-on Deodorant

1.6 fl. oz./ 50 ml